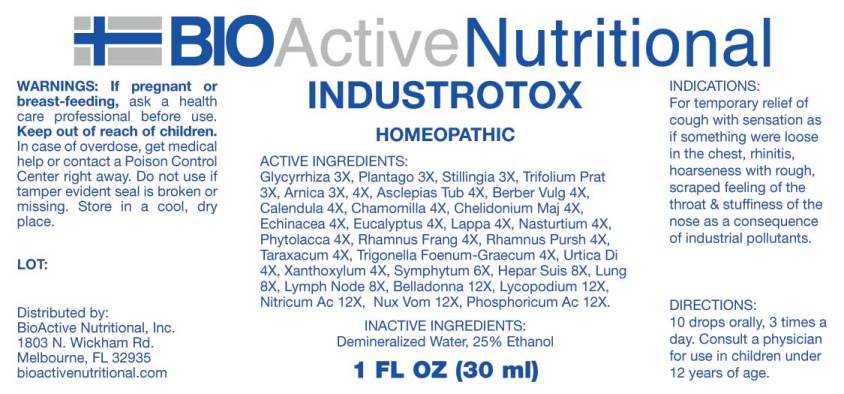 DRUG LABEL: Industrotox
NDC: 43857-0451 | Form: LIQUID
Manufacturer: BioActive Nutritional, Inc.
Category: homeopathic | Type: HUMAN OTC DRUG LABEL
Date: 20170616

ACTIVE INGREDIENTS: GLYCYRRHIZA GLABRA 3 [hp_X]/1 mL; PLANTAGO MAJOR 3 [hp_X]/1 mL; STILLINGIA SYLVATICA ROOT 3 [hp_X]/1 mL; TRIFOLIUM PRATENSE FLOWER 3 [hp_X]/1 mL; ARNICA MONTANA 3 [hp_X]/1 mL; ASCLEPIAS TUBEROSA ROOT 4 [hp_X]/1 mL; BERBERIS VULGARIS ROOT BARK 4 [hp_X]/1 mL; CALENDULA OFFICINALIS FLOWERING TOP 4 [hp_X]/1 mL; MATRICARIA RECUTITA 4 [hp_X]/1 mL; CHELIDONIUM MAJUS 4 [hp_X]/1 mL; ECHINACEA ANGUSTIFOLIA 4 [hp_X]/1 mL; EUCALYPTUS GLOBULUS LEAF 4 [hp_X]/1 mL; ARCTIUM LAPPA ROOT 4 [hp_X]/1 mL; NASTURTIUM OFFICINALE 4 [hp_X]/1 mL; PHYTOLACCA AMERICANA ROOT 4 [hp_X]/1 mL; FRANGULA ALNUS BARK 4 [hp_X]/1 mL; FRANGULA PURSHIANA BARK 4 [hp_X]/1 mL; TARAXACUM OFFICINALE 4 [hp_X]/1 mL; FENUGREEK SEED 4 [hp_X]/1 mL; URTICA DIOICA 4 [hp_X]/1 mL; ZANTHOXYLUM AMERICANUM BARK 4 [hp_X]/1 mL; COMFREY ROOT 6 [hp_X]/1 mL; PORK LIVER 8 [hp_X]/1 mL; SUS SCROFA LUNG 8 [hp_X]/1 mL; SUS SCROFA LYMPH 8 [hp_X]/1 mL; ATROPA BELLADONNA 12 [hp_X]/1 mL; LYCOPODIUM CLAVATUM SPORE 12 [hp_X]/1 mL; NITRIC ACID 12 [hp_X]/1 mL; STRYCHNOS NUX-VOMICA SEED 12 [hp_X]/1 mL; PHOSPHORIC ACID 12 [hp_X]/1 mL
INACTIVE INGREDIENTS: WATER; ALCOHOL

Drug Facts:

ACTIVE INGREDIENTS:

Glycyrrhiza Glabra 3X, Plantago Major 3X, Stillingia Sylvatica 3X, Trifolium Pratense 3X, Arnica Montana 3X, 4X, Asclepias Tuberosa 4X, Berberis Vulgaris 4X, Calendula Officinalis 4X, Chamomilla 4X, Chelidonium Majus 4X, Echinacea (Angustifolia) 4X, Eucalyptus Globulus 4X, Lappa Major 4X, Nasturtium Aquaticum 4X, Phytolacca Decandra 4X, Rhamnus Frangula 4X, Rhamnus Purshiana 4X, Taraxacum Officinale 4X, Trigonella Foenum-Graecum 4X, Urtica Dioica 4X, Xanthoxylum Fraxineum 4X, Symphytum Officinale 3X, Hepar Suis 8X, Lung (Suis) 8X, Lymph Node (Suis) 8X, Belladonna 12X, Lycopodium Clavatum 12X, Nitricum Acidum 12X, Nux Vomica 12X, Phosphoricum Acidum 12X.

HOMEOPATHIC INDICATIONS:

For temporary relief of cough with sensation as if something were loose in the chest, rhinitis, hoarseness with rough, scraped feeling of the throat & stuffiness of the nose as a consequence of industrial pollutants.**

**These statements are based upon homeopathic principles. They have not been reviewed by the Food and Drug Administration.

WARNINGS:

If pregnant or breast-feeding, ask a health care professional before use.

Keep out of reach of children. In case of overdose, get medical help or contact a Poison Control Center right away.

Do not use if tamper evident seal is broken or missing. Store in a cool, dry place.

Keep out of reach of children. In case of overdose, get medical help or contact a Poison Control Center right away.

DIRECTIONS:

10 drops orally, 3 times a day. Consult a physician for use in children under 12 years of age.

HOMEOPATHIC INDICATIONS:

For temporary relief of cough with sensation as if something were loose in the chest, rhinitis, hoarseness with rough, scraped feeling of the throat & stuffiness of the nose as a consequence of industrial pollutants.**

**These statements are based upon homeopathic principles. They have not been reviewed by the Food and Drug Administration.

INACTIVE INGREDIENTS:

Demineralized Water, 25% Ethanol

QUESTIONS:

Distributed by:

BioActive Nutritional, Inc.

1803 N. Wickham Rd.

Melbourne, FL 32935

PACKAGE LABEL DISPLAY:

BIOActive Nutritional

INDUSTROTOX

HOMEOPATHIC

1 FL OZ (30 ml)